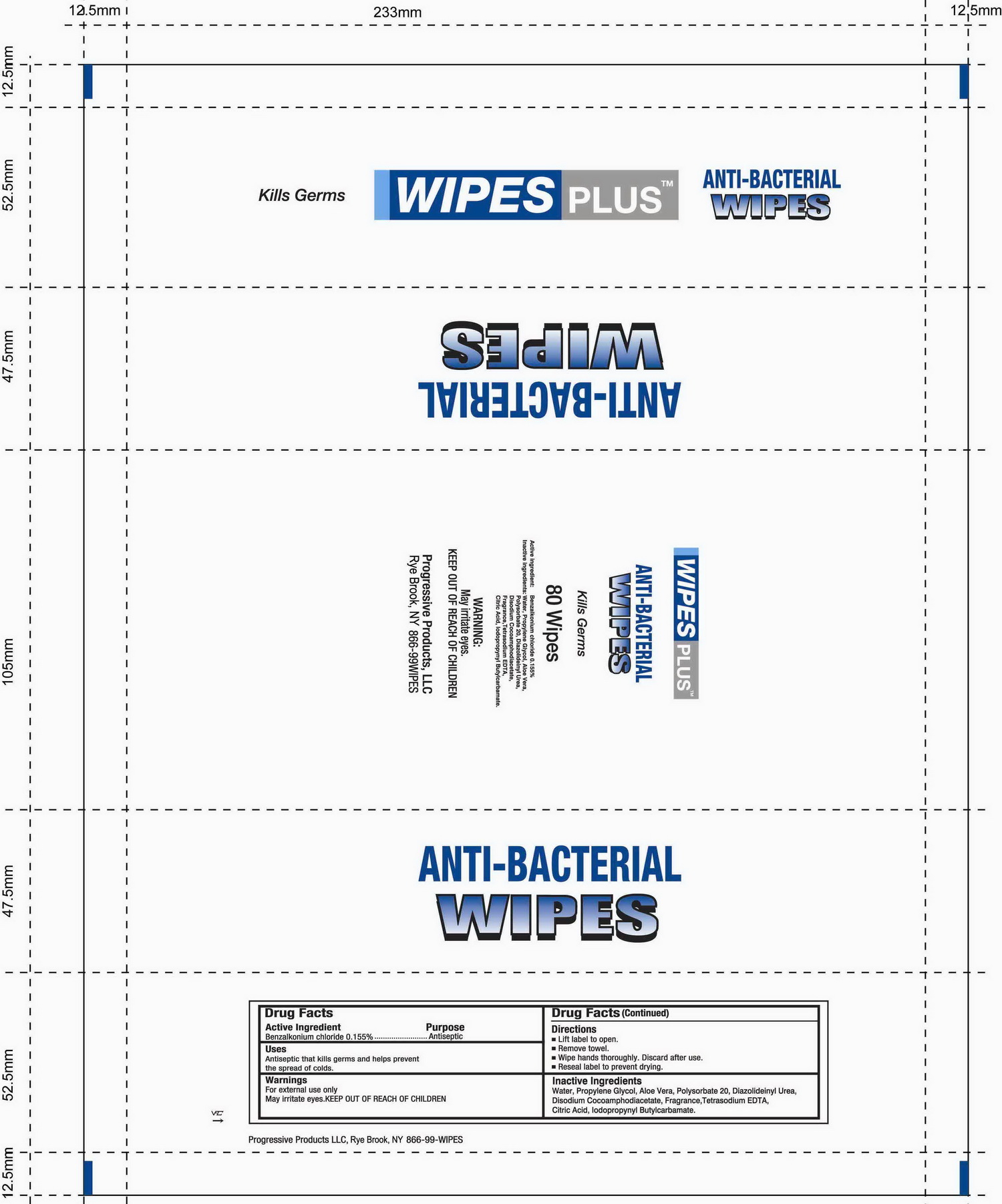 DRUG LABEL: Anti-Bacterial Wipes
NDC: 50552-002 | Form: SOLUTION
Manufacturer: Tongling Jieya Biological Technology Co., Ltd.
Category: otc | Type: HUMAN OTC DRUG LABEL
Date: 20250104

ACTIVE INGREDIENTS: BENZALKONIUM CHLORIDE 0.155 g/100 g
INACTIVE INGREDIENTS: WATER; PROPYLENE GLYCOL; POLYSORBATE 20; ALOE VERA LEAF; IODOPROPYNYL BUTYLCARBAMATE; EDETATE DISODIUM; ANHYDROUS CITRIC ACID

50552-002

Active Ingredient

Benzalkonium Chloride 0.155%

Purpose

Antiseptic

Uses

Antiseptic that kills germs and helps prevent the spread of cold

Warnings:

For external use only

May irritate eys. Keep out of reach of children.

Keep out of reach of children

Directions

- Lift label to open
- Remove towel
- Wipe hands thoroughly. Discard after use.
- Reseal label to prevent drying

Inactive Ingredients

Water, Propylene Glycol, Aloe Vera, Polysorbate 20, Diazolideinyl Urea, Disodium Cocoamphodiacetate, Fragrance, Tetrasodium EDTA, Citric Acid, Iodopropynyl Buylcarbamate